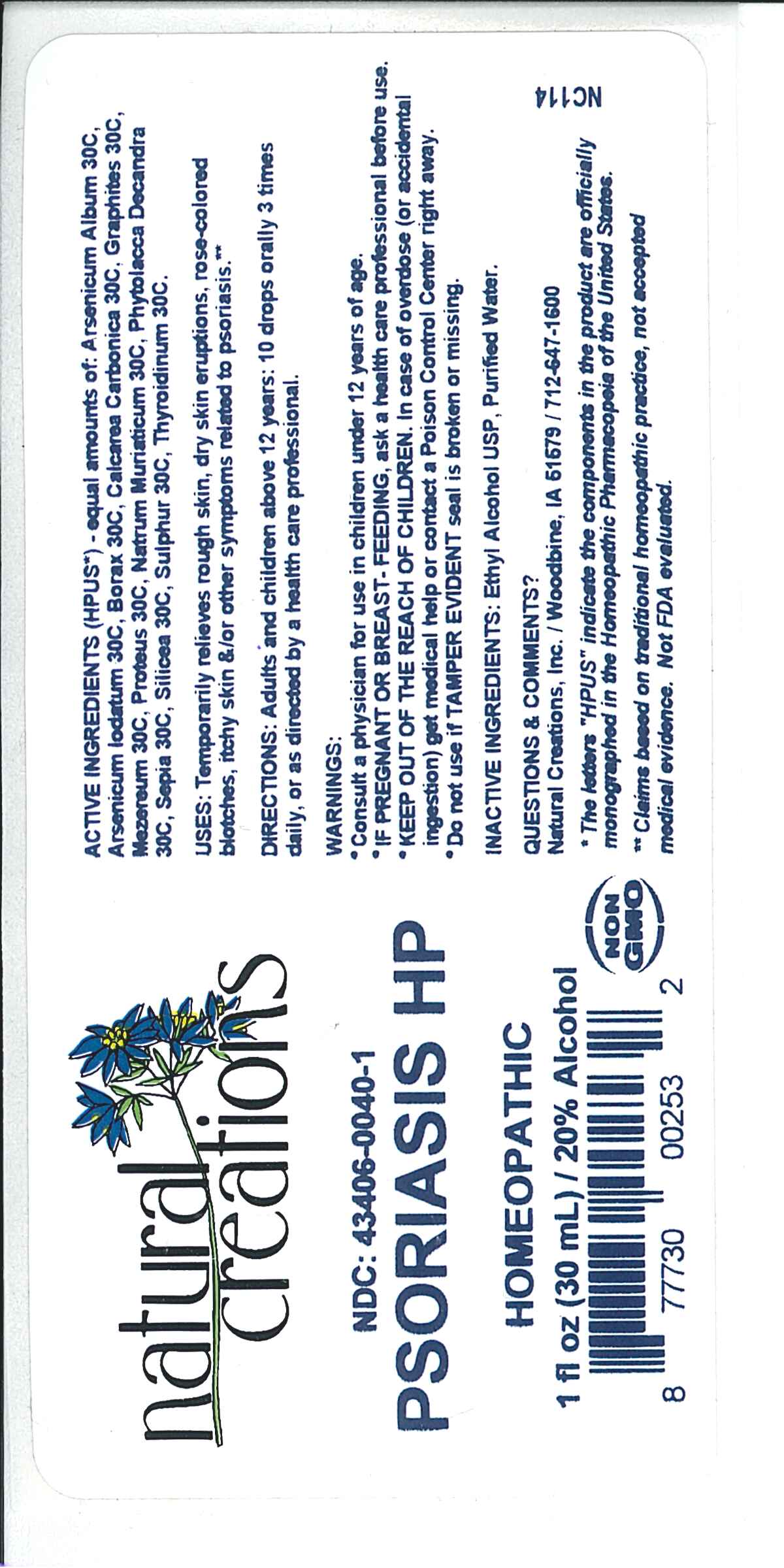 DRUG LABEL: PSORIASIS HP
NDC: 43406-0040 | Form: LIQUID
Manufacturer: Natural Creations, Inc.
Category: homeopathic | Type: HUMAN OTC DRUG LABEL
Date: 20251216

ACTIVE INGREDIENTS: ARSENIC TRIOXIDE 30 [hp_C]/1 mL; SODIUM BORATE 30 [hp_C]/1 mL; OYSTER SHELL CALCIUM CARBONATE, CRUDE 30 [hp_C]/1 mL; GRAPHITE 30 [hp_C]/1 mL; DAPHNE MEZEREUM BARK 30 [hp_C]/1 mL; PROTEUS MORGANII 30 [hp_C]/1 mL; SODIUM CHLORIDE 30 [hp_C]/1 mL; PHYTOLACCA AMERICANA ROOT 30 [hp_C]/1 mL; SEPIA OFFICINALIS JUICE 30 [hp_C]/1 mL; SULFUR 30 [hp_C]/1 mL; THYROID, UNSPECIFIED 30 [hp_C]/1 mL; ARSENIC TRIIODIDE 30 [hp_C]/1 mL
INACTIVE INGREDIENTS: WATER; ALCOHOL

PSORIASIS HP

ACTIVE INGREDIENT

ACTIVE INGREDIENTS (*HPUS) - equal amounts of: Arsenicum Album 30C, Arsenicum Iodatum 30C, Borax 30C, Calcarea Carbonica 30C, Graphites 30C, Mezereum 30C, Proteus 30C, Natrum Muriaticum 30C, Phytolacca Decandra 30C, Sepia 30C, Silica 30C, Sulphur 30C, Thyroidinum 30C

PURPOSE

USES: Temporarily relieves rough skin, dry skin eruptions, rose-colored blotches, itchy skin, &/or other symptoms related to psoriasis.**

INDICATIONS AND USAGE

USES: Temporarily relieves rough skin, dry skin eruptions, rose-colored blotches, itchy skin, &/or other symptoms related to psoriasis.**

DOSAGE AND ADMINISTRATION

DIRECTIONS: Adults and children above 12 years: 10 drops orally 3 times daily, or as directed by a health care professional.

KEEP OUT OF REACH OF CHILDREN

KEEP OUT OF THE REACH OF CHILDREN. In case of overdose (or accidental ingestion) get medical help or contact a Poison Control Center right away.

WARNINGS:

*Consult a physician for use in children under 12 years of age.

* IF PREGNANT OR BREAST-FEEDING, ask a health care professional before use.

* KEEP OUT OF THE REACH OF CHILDREN. In case of overdose (or accidental ingestion) get medical help or contact a Poison Control Center right away.

Inactive Ingredients: Purified Water, USP Ethanol Alcohol 20%

Other Information: Tamper Seal: “Sealed for your protection.” Do not use if seal is broken or missing.

QUESTIONS

Questions & Comments? Natural Creations, Inc. / Woodbine, IA 51579 / 712-647-1600

REFERENCES

*The letters "HPUS" indicate the components in the product are officially monographed in the Homeopathic Pharmacopeia of the United States.

**Claims based on traditional homeopathic practice, not accepted medical evidence. Not FDA evaluated.

PACKAGE LABEL

NDC: 43406-0040-1

PSORIASIS HP

HOMEOPATHIC

1 fl oz (30 mL) / 20% Alcohol